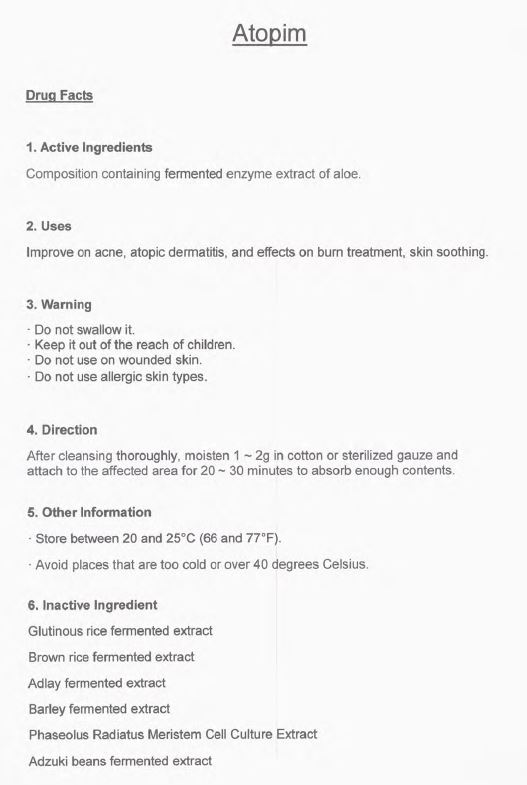 DRUG LABEL: ATOPIM
NDC: 73158-0001 | Form: LIQUID
Manufacturer: HI Technology
Category: otc | Type: HUMAN OTC DRUG LABEL
Date: 20190610

ACTIVE INGREDIENTS: GLYCERIN 2.5 g/100 g; ALOE 64 g/100 g
INACTIVE INGREDIENTS: BUTYLENE GLYCOL; NIACINAMIDE

Drug Facts

ACTIVE INGREDIENT

aloe, glycerin

INACTIVE INGREDIENT

butylene glycol, water, niacinamide, adlay fermented extract, etc

PURPOSE

improve on acne, stopic dermatitis, and effects on burn treatment, skin soothing

keep out of reach of the children

INDICATIONS AND USAGE

after cleansing thoroughly, moisten 1~2g in cotton or sterilized gauze and attached to the affected area for 20~30 minutes to absorb enough contents

WARNINGS

do not swallow it

do not use on wounded skin

do not use allergic skin types

DOSAGE AND ADMINISTRATION

for topical use only